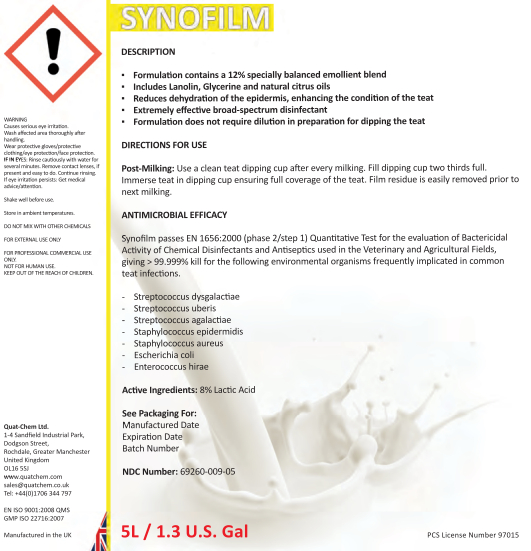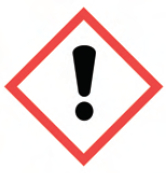 DRUG LABEL: Synofilm
NDC: 69260-009 | Form: LIQUID
Manufacturer: Quat-Chem Ltd.
Category: animal | Type: OTC ANIMAL DRUG LABEL
Date: 20160316

ACTIVE INGREDIENTS: LACTIC ACID 80 g/1 L

Synofilm

Synofilm

WARNING
Causes serious eye irritation.
Wash affected area thoroughly after handling.
Wear protective gloves/protective clothing/eye protection/face protection.
IF IN EYES: Rinse cautiously with water for several minutes. Remove contact lenses, if present and easy to do. Continue rinsing.
If eye irritation persists: Get medical advice/attention.
Shake well before use.
Store in ambient temperatures.

DO NOT MIX WITH OTHER CHEMICALS
FOR EXTERNAL USE ONLY
FOR PROFESSIONAL COMMERCIAL USE
ONLY.
NOT FOR HUMAN USE.
KEEP OUT OF THE REACH OF CHILDREN.

Quat-Chem Ltd.
1-4 Sandfield Industrial Park,
Dodgson Street,
Rochdale, Greater Manchester
United Kingdom
OL16 5SJ
www.quatchem.com
sales@quatchem.co.uk
Tel: +44(0)1706 344 797

EN ISO 9001:2008 QMS
GMP ISO 22716:2007

Manufactured in the UK

DESCRIPTION
▪ Formulation contains a 12% specially balanced emollient blend
▪ Includes Lanolin, Glycerine and natural citrus oils
▪ Reduces dehydration of the epidermis, enhancing the condition of the teat
▪ Extremely effective broad-spectrum disinfectant
▪ Formulation does not require dilution in preparation for dipping the teat

DIRECTIONS FOR USE
Post-Milking: Use a clean teat dipping cup after every milking. Fill dipping cup two thirds full.
Immerse teat in dipping cup ensuring full coverage of the teat. Film residue is easily removed prior to next milking.

ANTIMICROBIAL EFFICACY
Synofilm passes EN 1656:2000 (phase 2/step 1) Quantitative Test for the evaluation of Bactericidal Activity of Chemical Disinfectants and Antiseptics used in the Veterinary and Agricultural Fields,
giving > 99.999% kill for the following environmental organisms frequently implicated in common
teat infections.
- Streptococcus dysgalactiae
- Streptococcus uberis
- Streptococcus agalactiae
- Staphylococcus epidermidis
- Staphylococcus aureus
- Escherichia coli
- Enterococcus hirae

Active Ingredients: 8% Lactic Acid

See Packaging For:
Manu Manufactured Date
Expiration Date
Batch Numbe

NDC Number: